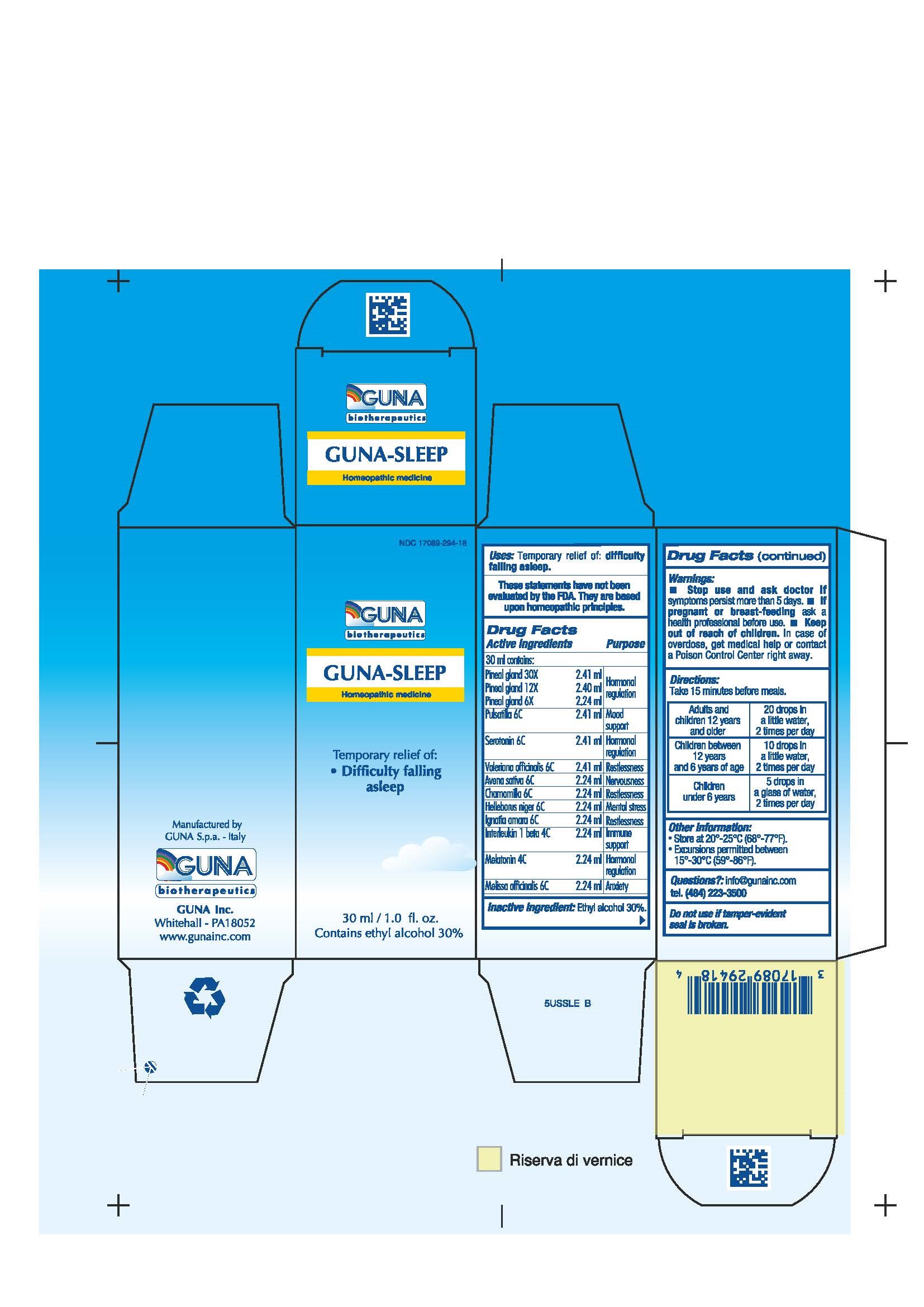 DRUG LABEL: GUNA-SLEEP
NDC: 17089-294 | Form: SOLUTION/ DROPS
Manufacturer: Guna spa
Category: homeopathic | Type: HUMAN OTC DRUG LABEL
Date: 20181221

ACTIVE INGREDIENTS: AVENA SATIVA FLOWERING TOP 6 [hp_C]/30 mL; CHAMOMILE 6 [hp_C]/30 mL; HELLEBORUS NIGER ROOT 6 [hp_C]/30 mL; STRYCHNOS IGNATII SEED 6 [hp_C]/30 mL; CANAKINUMAB 4 [hp_C]/30 mL; MELATONIN 4 [hp_C]/30 mL; MELISSA OFFICINALIS 6 [hp_C]/30 mL; SUS SCROFA PINEAL GLAND 12 [hp_X]/30 mL; PULSATILLA VULGARIS 6 [hp_C]/30 mL; SEROTONIN 6 [hp_C]/30 mL; VALERIAN 6 [hp_C]/30 mL
INACTIVE INGREDIENTS: ALCOHOL

GUNA-SLEEP

ACTIVE INGREDIENT

Avena sativa 6C Nervousness
Chamomilla 6C Restlessness
Helleborus niger 6C Mental stress
Ignatia amara 6C Restlessness
Interleukin 1 beta 4C Immune support
Melatonin 4C Hormonal regulation
Melissa officinalis 6C Anxiety
Pineal gland 6X 12X 30X Hormonal regulation
Pulsatilla 6C Mood support
Serotonin 6C Hormonal support
Valeriana officinalis 6C Restlessness

PURPOSE

Temporary relief of:

- Difficulty falling asleep

- Stop use and ask doctor if symptoms persist more than 5 days.
- If pregnant or breast-feeding ask a health professional before use.
- Keep out of reach of children. In case of overdose, get medical help or contact a Poison Control Center right away.
- Contains ethyl alcohol 30%

PREGNANCY OR BREAST FEEDING

If pregnant or breast-feeding ask a doctor before use

Keep out of reach of children

DOSAGE AND ADMINISTRATION

Adults and children 12 years and older 20 drops in a little water, 2 times per day
Children between 12 years and 6 years of age 10 drops in a little water, , 2 times per day
Children under 6 years 5 drops in a glass of water, , 2 times per day

Questions?: info@gunainc.com
Tel. (484) 223-3500

inactive ingredient: Ethyl alcohol 30%.

INDICATIONS AND USAGE

Take 15 minutes before meals.